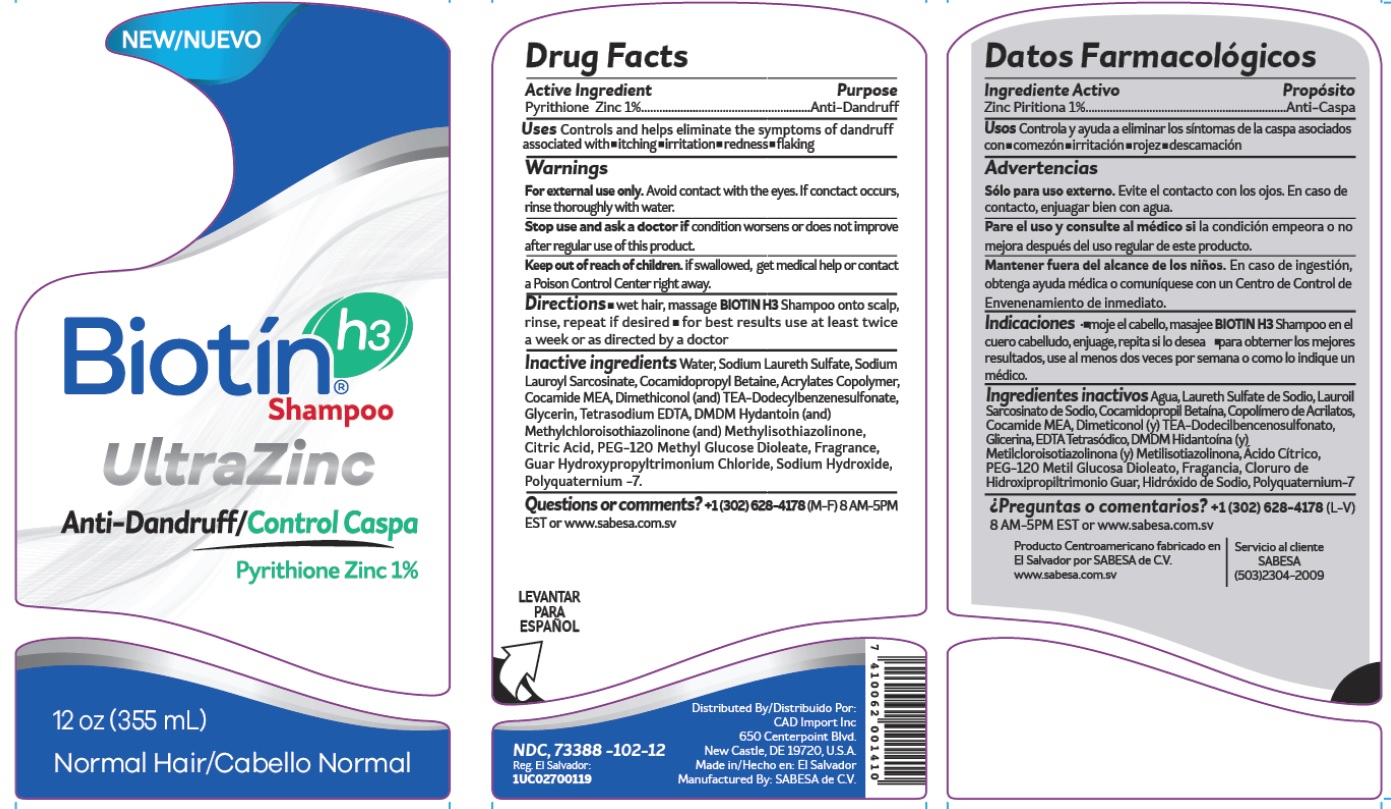 DRUG LABEL: Biotin H3 Anti-Dandruff Normal
NDC: 73388-102 | Form: SHAMPOO
Manufacturer: Salones de Belleza y Equipos de El Salvador Sociedad Anonima de Capital Variable
Category: otc | Type: HUMAN OTC DRUG LABEL
Date: 20210114

ACTIVE INGREDIENTS: PYRITHIONE ZINC 0.01 g/1 mL
INACTIVE INGREDIENTS: SODIUM HYDROXIDE; WATER; SODIUM LAURETH SULFATE; COCAMIDOPROPYL BETAINE; SODIUM LAUROYL SARCOSINATE; COCO MONOETHANOLAMIDE; DIMETHICONOL (100000 CST); BUTYL ACRYLATE/METHYL METHACRYLATE/METHACRYLIC ACID COPOLYMER (18000 MW); TRIETHANOLAMINE DODECYLBENZENESULFONATE; METHYLISOTHIAZOLINONE; CITRIC ACID MONOHYDRATE; DMDM HYDANTOIN; METHYLCHLOROISOTHIAZOLINONE; PEG-120 METHYL GLUCOSE DIOLEATE; POLYQUATERNIUM-7 (70/30 ACRYLAMIDE/DADMAC; 1600 KD); EDETATE SODIUM; GUAR HYDROXYPROPYLTRIMONIUM CHLORIDE (1.7 SUBSTITUENTS PER SACCHARIDE); GLYCERIN

Biotin H3 Anti-Dandruff Shampoo Normal

Active Ingredient

Active ingredient | Purpose
Pyrithione Zinc 1% ………………………………………. | Anti-dandruff

Uses

Controls and helps eliminate the symptoms of dandruff asoiciated with

- itching
- irritation
- redness
- flaking

Warnings

For external uses only. Avoid contact with the eyes. If conctact occurs, rinse thoroughly with water.

Stop use and ask a doctor if

condition worsens or does not improve after regular use of this product.

Keep out of reach of children.

if swallowed, get medical help or contact a Poison Control Center right away.

Directions

wet hair, massage BIOTIN H3 Shampoo onto scalp, rinse, repeat if desired • for best results use at least twice a week or as directed by a doctor

Inactive Ingredient

Water, Sodium Laureth Sulfate, Sodium Lauroyl Sarcosinate, Cocamidopropyl Betaine, Acrylates Copolymer, Cocamide MEA, Dimethiconol (and) TEA-Dodecylbenzenesulfonate, Glycerin, Tetrasodium EDTA, DMDM Hydantoin (and) Methylchloroisothiazolinone (and) Methylisothiazolinone, Citric Acid, PEG-120 Methyl Glucose Dioleate, Fragrance, Guar Hydroxypropyltrimonium Chloride, Sodium Hydroxide, Polyquaternium -7

Questions or comments?

+1-302-628-4178 (M-F) 8 AM-5PM EST or www.sabesa.com.sv

Prinicipal Display Panel

New/Nuevo

Biotin H3

UltraZinc

Anti-Dandruff/Control Caspa

Pyrithione Zinc 1%

12 oz (355 mL)

Normal Hair/Cabello Normal